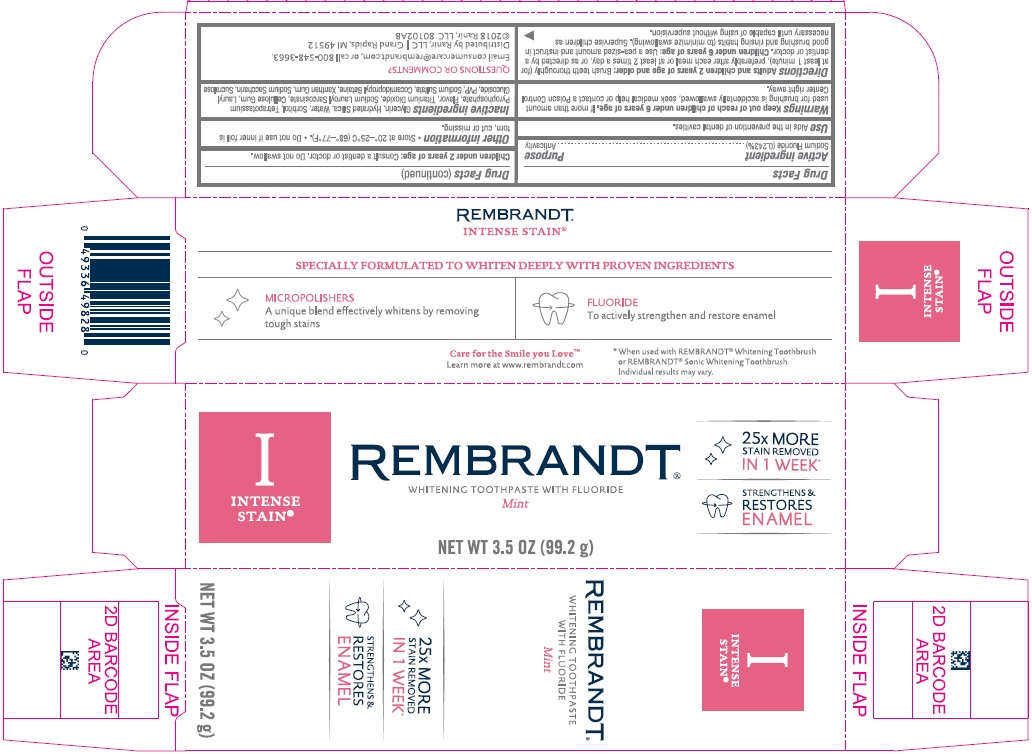 DRUG LABEL: Rembrandt Intense Stain
NDC: 66923-373 | Form: PASTE, DENTIFRICE
Manufacturer: Ranir LLC
Category: otc | Type: HUMAN OTC DRUG LABEL
Date: 20241126

ACTIVE INGREDIENTS: SODIUM FLUORIDE 24.3 mg/1 g
INACTIVE INGREDIENTS: GLYCERIN; HYDRATED SILICA; WATER; SORBITOL; POTASSIUM PYROPHOSPHATE; TITANIUM DIOXIDE; SODIUM LAUROYL SARCOSINATE; CARBOXYMETHYLCELLULOSE SODIUM, UNSPECIFIED; LAURYL GLUCOSIDE; POVIDONE, UNSPECIFIED; SODIUM SULFATE; COCAMIDOPROPYL BETAINE; XANTHAN GUM; SACCHARIN SODIUM; SUCRALOSE

373 Rembrandt Intense Stain Mint Whitening Toothpaste

Active ingredient

Sodium Fluoride (0.243%)

Purpose

Anticavity

Use

Aids in the prevention of dental cavities.

Keep out of reach of children under 6 years of age.

If more than amount used for brushing is accidentally swallowed, seek medical help or contact a Poison Control Center right away.

Directions

Adults and children 2 years of age and older: Brush teeth thoroughly (for at least 1 minute), preferably after each meal or at least 2 times a day, or as directed by a dentist or doctor.

Children under 6 years of age: Use a pea-sized amount and instruct in good brushing and rinsing habits (to minimize swallowing). Supervise children as necessary until capable of using without supervision.

Children under 2 years of age: Consult a dentist or doctor. Do not swallow.

Other information

- Store at 20°-25°C (68°-77°F).
- Do not use if inner foil is torn, cut or missing.

Inactive ingredients

Glycerin, Hydrated Silica, Water, Sorbitol, Tetrapotassium Pyrophosphate, Flavor, Titanium Dioxide, Sodium Lauroyl Sarcosinate, Cellulose Gum, Lauryl Glucoside, PVP, Sodium Sulfate, Cocamidopropyl Betaine, Xanthan Gum, Sodium Saccharin, Sucralose.

QUESTIONS OR COMMENTS?

Email consumercare@rembrandt.com, or call 800-548-3663.

Distributed by Ranir, LLC,

Grand Rapids, MI 49512

©2018 Ranir, LLC 80102AB

Directions: updated use instructions 7/2/2019

Principal Display Panel

I INTENSE STAIN®

REMBRANDT

WHITENING TOOTHPASTE WITH FLUORIDE

Mint

25x MORE STAIN REMOVED IN 1 WEEK

STRENGTHENS & RESTORES ENAMEL

NET WT 3.5 OZ (99.2 g)